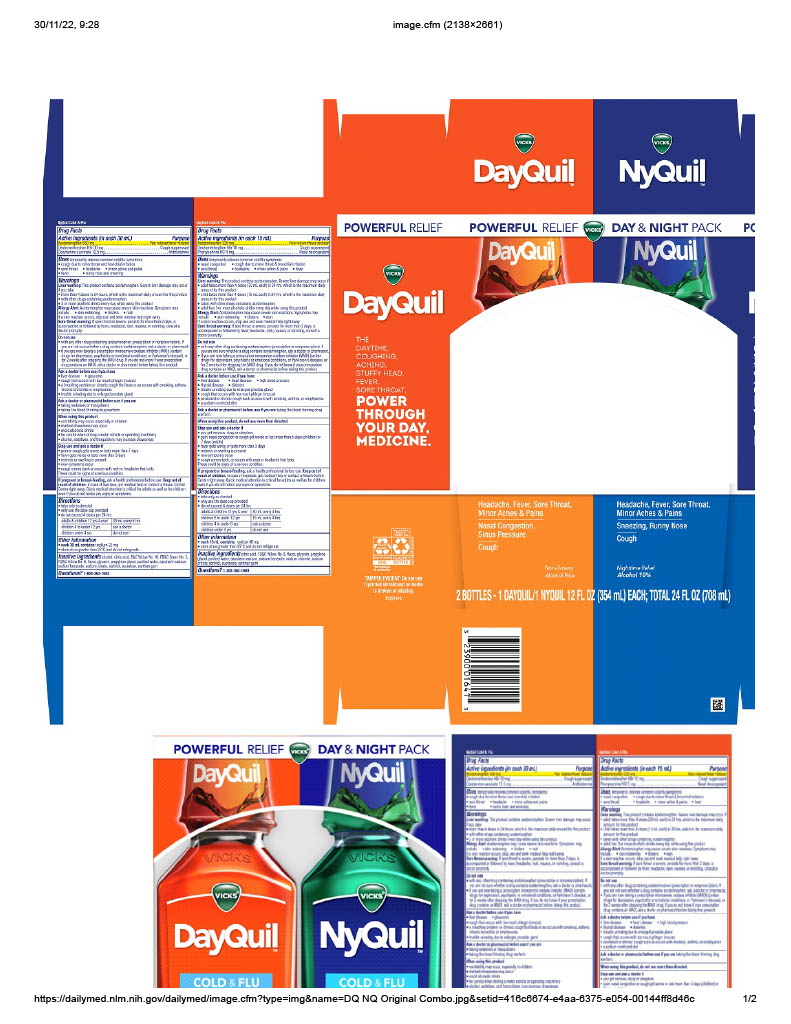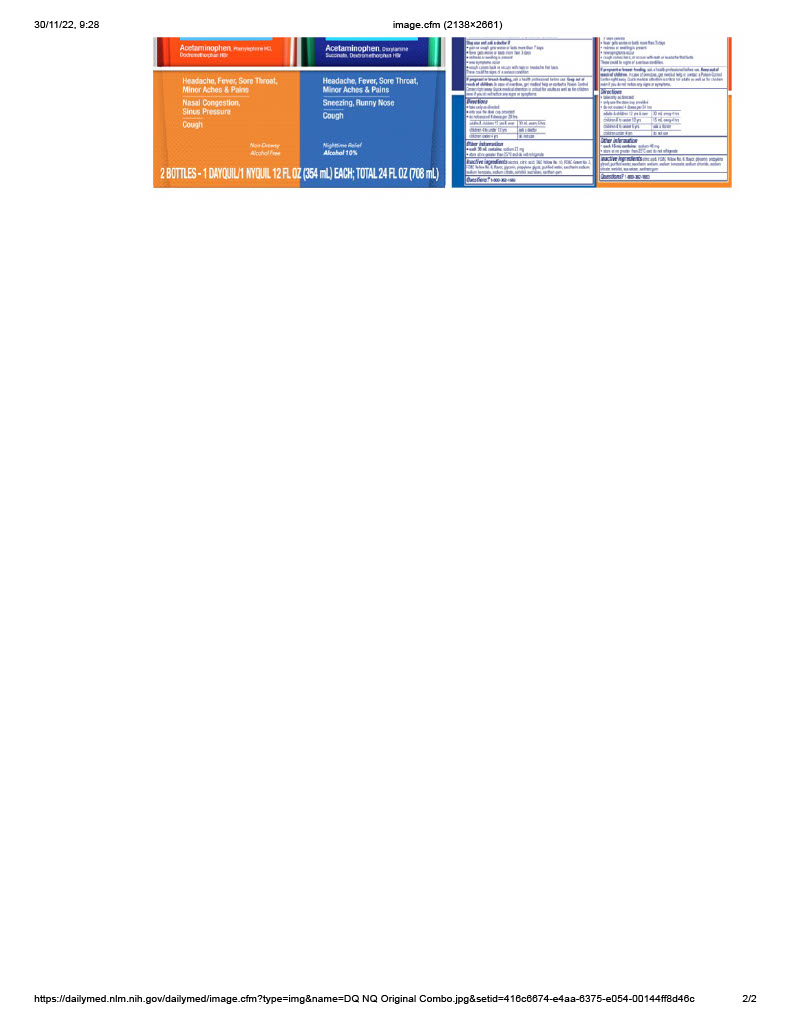 DRUG LABEL: Nighttime Cold and Flu
NDC: 81660-777 | Form: LIQUID
Manufacturer: Grimann, S.A. de C.V.
Category: otc | Type: HUMAN OTC DRUG LABEL
Date: 20260126

ACTIVE INGREDIENTS: DEXTROMETHORPHAN HYDROBROMIDE 30 mg/30 mL; DOXYLAMINE SUCCINATE 12.5 mg/30 mL; ACETAMINOPHEN 650 mg/30 mL
INACTIVE INGREDIENTS: WATER 1 mg/30 mL; SACCHARIN SODIUM 1 mg/30 mL; SODIUM BENZOATE 1 mg/30 mL; SODIUM CITRATE 1 mg/30 mL; SUCRALOSE 1 mg/30 mL; PROPYLENE GLYCOL 1 mg/30 mL; ALCOHOL 1 mg/30 mL; D&C YELLOW NO. 10 1 mg/30 mL; GLYCERIN 1 mg/30 mL; SORBITOL 1 mg/30 mL; CITRIC ACID ACETATE 1 mg/30 mL; FD&C BLUE NO. 1 1 mg/30 mL

DOSAGE AND ADMINISTRATION

take only as directed

only use the dose cup provided
do not exceed 4 doses per 24 hrs

adults & children 12 yrs & over

30 mL every 6 hrs

children 4 to under 12 yrs

ask a doctor

children under 4 yrs

do not use

Warnings

Liver warning: This product contains acetaminophen. Severe liver damage may occur if you take

more than 4 doses in 24 hrs, which is the maximum daily amount for this product
with other drugs containing acetaminophen
3 or more alcoholic drinks every day while using this product

Allergy Alert: Acetaminophen may cause severe skin reactions.

Symptoms may include:

skin reddening
blisters
rash

If skin reaction occurs, stop use and seek medical help right away

Sore throat warning: If sore throat is severe, persist for more than 2 days, is accompanied or followed by fever, headache, rash, nausea, or vomiting, consult a doctor promptly.

INACTIVE INGREDIENT

Inactive ingredients alcohol, citric acid, D&C Yellow No. 10, FD&C Blue No.1, flavor, glycerin, propylene glycol, purified water, saccharin sodium, sodium benzoate, sodium citrate, sorbitol, sucralose

Directions

take only as directed
only use the dose cup provided
do not exceed 4 doses per 24 hrs

adults & children 12 yrs & over

30 mL every 6 hrs

children 4 to under 12 yrs

ask a doctor

children under 4 yrs

do not use

KEEP OUT OF REACH OF CHILDREN

If pregnant or breast-feeding, ask a health professional before use. Keep out of reach of children. In case of overdose, get medical help or contact a Poison Control Center right away. Quick medical attention is critical for adults as well as for children even if you do not notice any signs or symptoms

Uses

temporarily relieves common cold/flu symptoms:

cough due to minor throat & bronchial irritation
sore throat
headache
minor aches & pains
fever

runny nose and sneezing

Active Ingredients (in each 30 mL) Purpose

Acetaminophen 650 mg……………………………………………………………………………………………………………….……….. Pain reliever/fever reducer

Dextromethorphan HBr 30 mg…………………………………………………………………………………………………….….………….……. Cough suppressant

Doxylamine succinate 12.5 mg………………………………………………………………………………………………………………………….……. Antihistamine